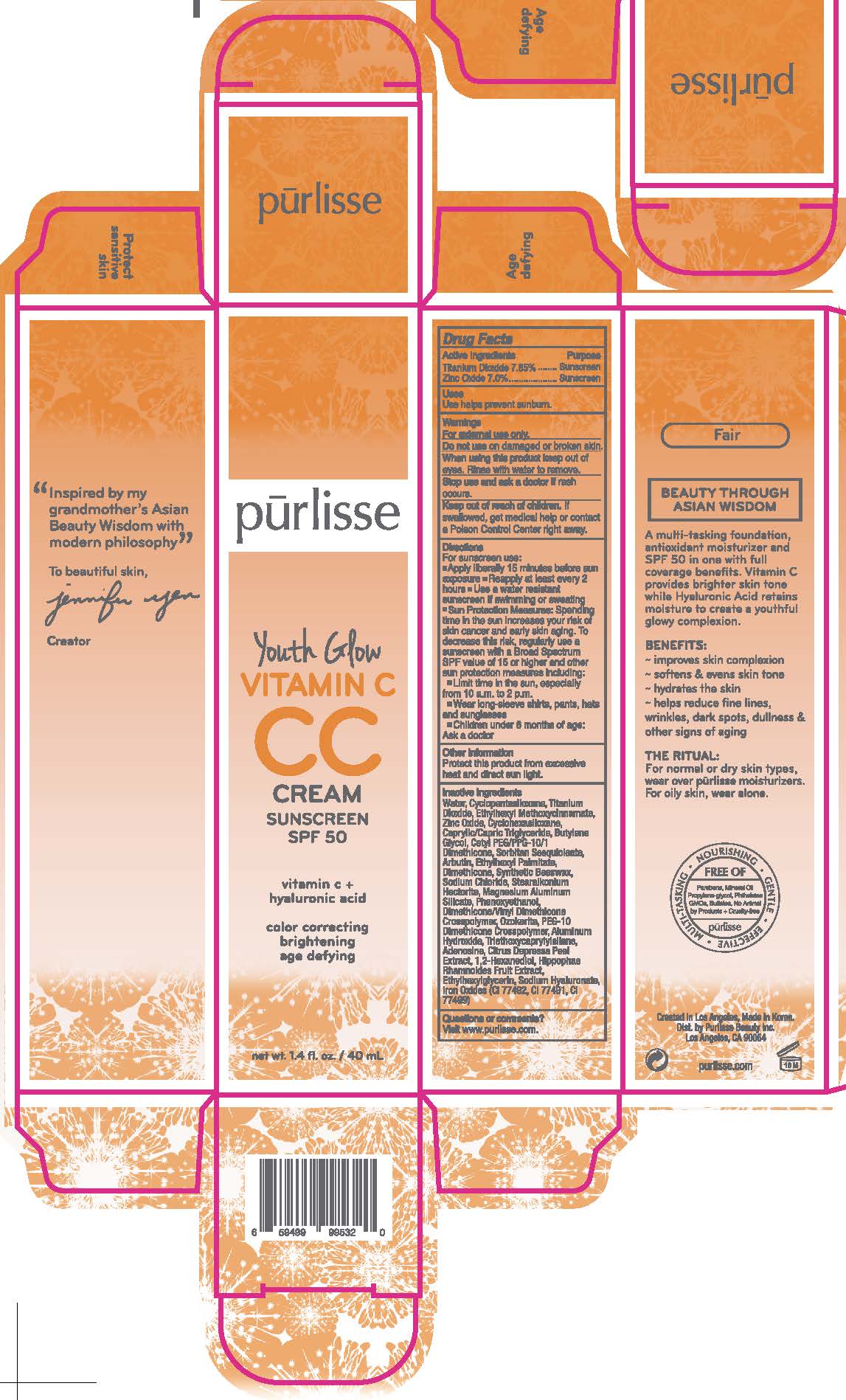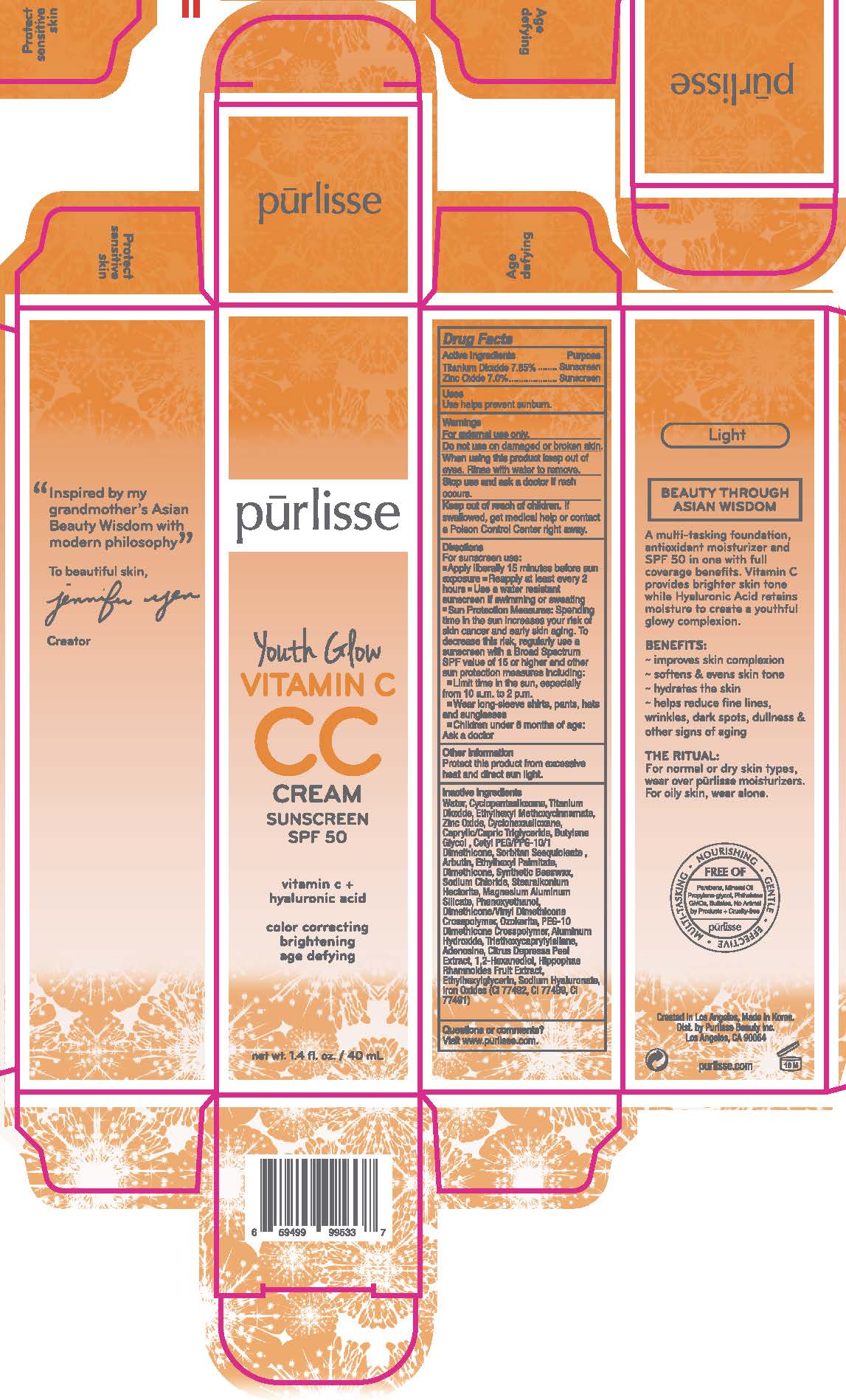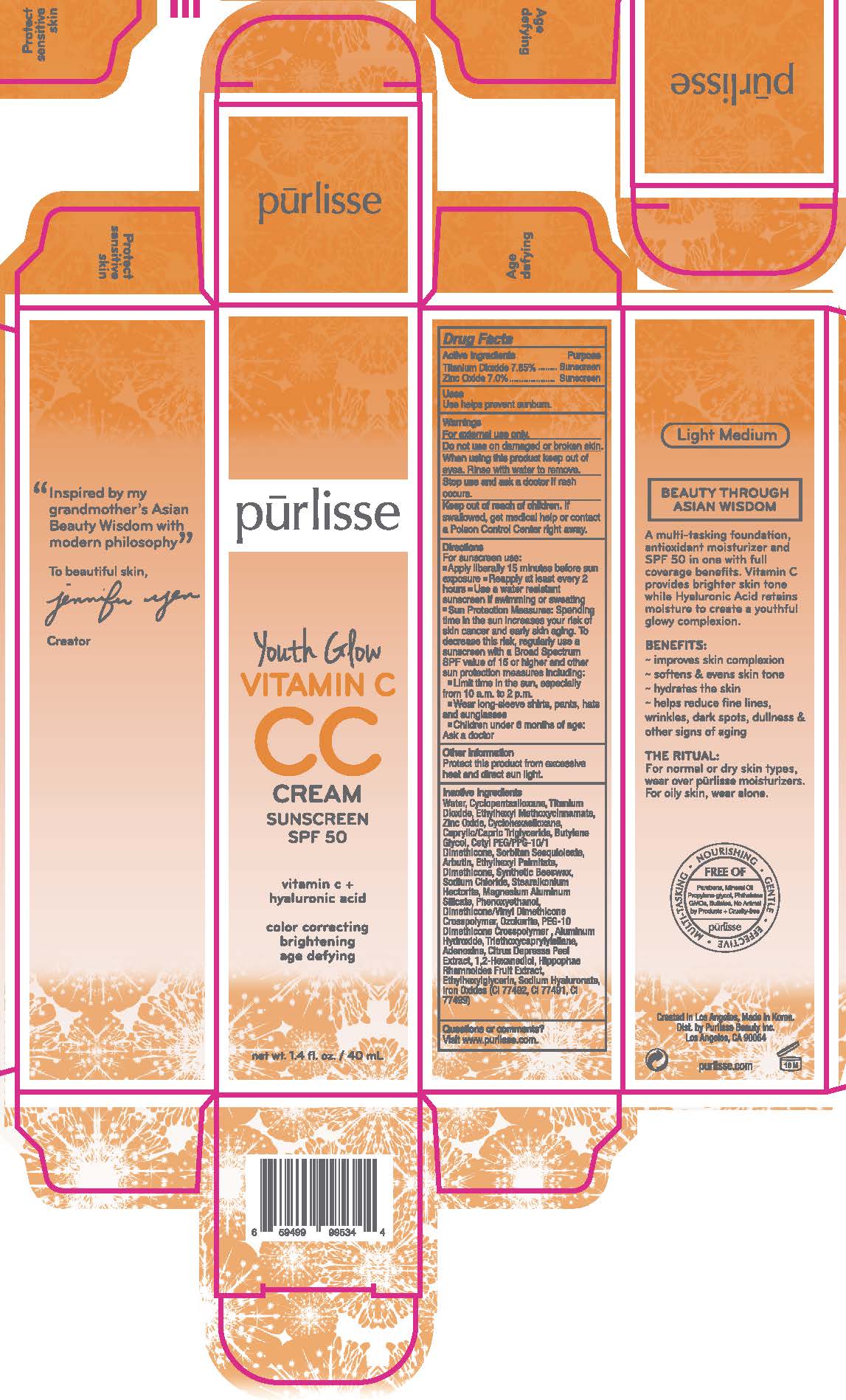 DRUG LABEL: Youth Glow Vitamin C CC Cream Sunscreen SPF 50 - Fair
NDC: 72407-431 | Form: CREAM
Manufacturer: Pur-lisse Beauty, LLC
Category: otc | Type: HUMAN OTC DRUG LABEL
Date: 20251231

ACTIVE INGREDIENTS: ZINC OXIDE 7 g/100 mL; TITANIUM DIOXIDE 9.8 g/100 mL; OCTINOXATE 7.5 g/100 mL
INACTIVE INGREDIENTS: ETHYLHEXYL PALMITATE; SORBITAN SESQUIOLEATE; WATER; ALUMINUM HYDROXIDE; CETYL PEG/PPG-10/1 DIMETHICONE (HLB 2); CAPRYLIC/CAPRIC TRIGLYCERIDE; DIMETHICONE/VINYL DIMETHICONE CROSSPOLYMER (SOFT PARTICLE); BUTYLENE GLYCOL; TANGERINE PEEL; 1,2-HEXANEDIOL; DIMETHICONE; SYNTHETIC BEESWAX; CERESIN; STEARALKONIUM HECTORITE; PHENOXYETHANOL; ADENOSINE; CYCLOPENTASILOXANE; PEG-10 DIMETHICONE (600 CST); HIPPOPHAE RHAMNOIDES FRUIT; ETHYLHEXYLGLYCERIN; TRIETHOXYCAPRYLYLSILANE; FERROUS OXIDE; CYCLOHEXASILOXANE; ARBUTIN; SODIUM CHLORIDE; MAGNESIUM ALUMINUM SILICATE; SODIUM HYALURONATE

Drug Facts

Active Ingredients

Octinoxate 7.5%

Titanium Dioxide 9.8%

Zinc Oxide 7.0%

Purpose

Sunscreen

Uses

Use helps prevent sunburn.

Warnings

For external use only.

Do not use on damage or broken skin.

When using this product keep out of eyes. Rinse with water to remove.

Stop use and ask a doctor if rash occurs.

Keep out of reach of children. If swallowed, get medical help or contact a Poison Control Center right away.

Directions

For sunscreen use:

- Apply liberally 15 minutes before sun exposure
- Reapply at least every 2 hours
- Use a water resistant sunscreen if swimming or sweating
- Sun Protection Measures: Spending time in the sun increases your risk of skin cancer and early skin aging. To decrease this risk, regularly use a sunscreen with a Broad Spectrum SPF value of 15 or higher and other sun protection measures including:
- Limit time in the sun, especially from 10 a.m. to 2 p.m.
- Wear long-sleeve shirts, pants, hats and sunglasses
- Children under 6 months of age: Ask a doctor

Other Information

Protect this product from excessive heat and direct sun light.

Inactive Ingredients

Water, Cyclopentasiloxane, Cyclohexasiloxane, Caprylic/Capric Triglyceride, Butylene Glycol, Cetyl PEG/PPG-10/1 Dimethicone, Sorbitan Sesquioleate, Arbutin, Ethylhexyl Palmitate, Dimethicone, Synthetic Beeswax, Sodium Chloride, Stearalkonium Hectorite, Magnesium Aluminum Silicate, Phenoxyethanol, Dimethicone/Vinyl Dimethicone Crosspolymer, Ozokerite, PEG-10 Dimethicone Crosspolymer, Aluminum Hydroxide, Triethoxycaprylylsilane, Adenosine, Citrus Depressa Peel Extract, 1,2-Hexanediol, Hippophae Rhamnoides Fruit Extract, Ethylhexylglycerin, Sodium Hyaluronate, Iron Oxides (CI 77492, CI 77491, CI 77499)

Questions or comments?

Visit www.purlisse.com.

Principal Display Panel - Youth Glow Vitamin C CC Cream Sunscreen SPF 50 - Fair

pūrlisse

Youth Glow

VITAMIN C

CC

CREAM

SUNSCREEN

SPF 50

vitamin c +

hyaluronic acid

color correcting

brightening

age defying

net wt. 1.4 fl. oz. / 40 mL

Principal Display Panel – Youth Glow Vitamin C CC Cream Sunscreen SPF 50 - Light

pūrlisse

Youth Glow

VITAMIN C

CC

CREAM

SUNSCREEN

SPF 50

vitamin c +

hyaluronic acid

color correcting

brightening

age defying

net wt. 1.4 fl. oz. / 40 mL

Principal Display Panel – Youth Glow Vitamin C CC Cream Sunscreen SPF 50 - Light Medium

pūrlisse

Youth Glow

VITAMIN C

CC

CREAM

SUNSCREEN

SPF 50

vitamin c +

hyaluronic acid

color correcting

brightening

age defying

net wt. 1.4 fl. oz. / 40 mL